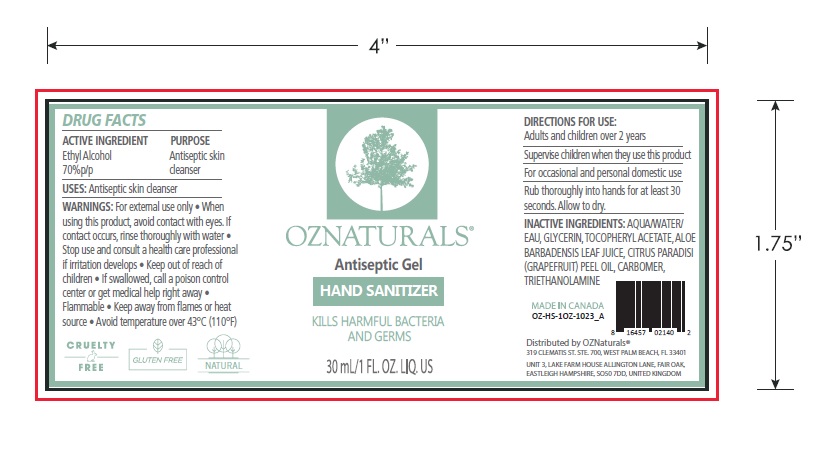 DRUG LABEL: OZ NATURALS Antiseptic Gel Handsanitizer
NDC: 75592-201 | Form: GEL
Manufacturer: OZ Naturals LLC
Category: otc | Type: HUMAN OTC DRUG LABEL
Date: 20211206

ACTIVE INGREDIENTS: ALCOHOL 70 mL/100 mL
INACTIVE INGREDIENTS: CITRUS PARADISI FRUIT OIL; CARBOMER 940; GLYCERIN; ALPHA-TOCOPHEROL ACETATE; WATER; ALOE VERA LEAF; TRIETHANOLAMINE ISOSTEARATE

OZ NATURALS Antiseptic Gel Handsanitizer

PURPOSE

Antispetic Skin Cleanser

Use

Antiseptic skin cleanser to help reduce bacteria that potentially can cause disease. For use when soap and water are not available.

DIRECTIONS FOR USE:

Adults and children over 2 years
Supervise children when they use this product
For occasional and personal domestic use
Rub thoroughly into hands for at least 30 seconds. Allow to dry.

ACTIVE INGREDIENT

Ethyl Alcohol 70%p/p

WARNINGS:

For external use only

• When using this product, avoid contact with eyes. If contact occurs, rinse thoroughly with water

• Stop use and consult a health care professional if irritation develops

• Keep out of reach of children

• If swallowed, call a poison control center or get medical help right away

• Flammable

• Keep away from flames or heat source

• Avoid temperature over 43°C (110°F)

Warnings

Keep out of reach of children

INACTIVE INGREDIENTS:

Aqua/Water/Eau, Glycerin, Tocopheryl Acetate, Aloe Barbadensis Leaf Juice, Citrus Paradisi (Grapefruit) Peel Oil, Carbomer, Triethanolamine

Distributed by OZNaturals®

319 Clematis St. Ste. 700,
West Palm Beach, FL 33401

MADE IN CANADA

Principal Display Panel

OZNATURALS Antiseptic Gel Hand Sanitizer

KILLS HARMFUL BACTERIA AND GERMS